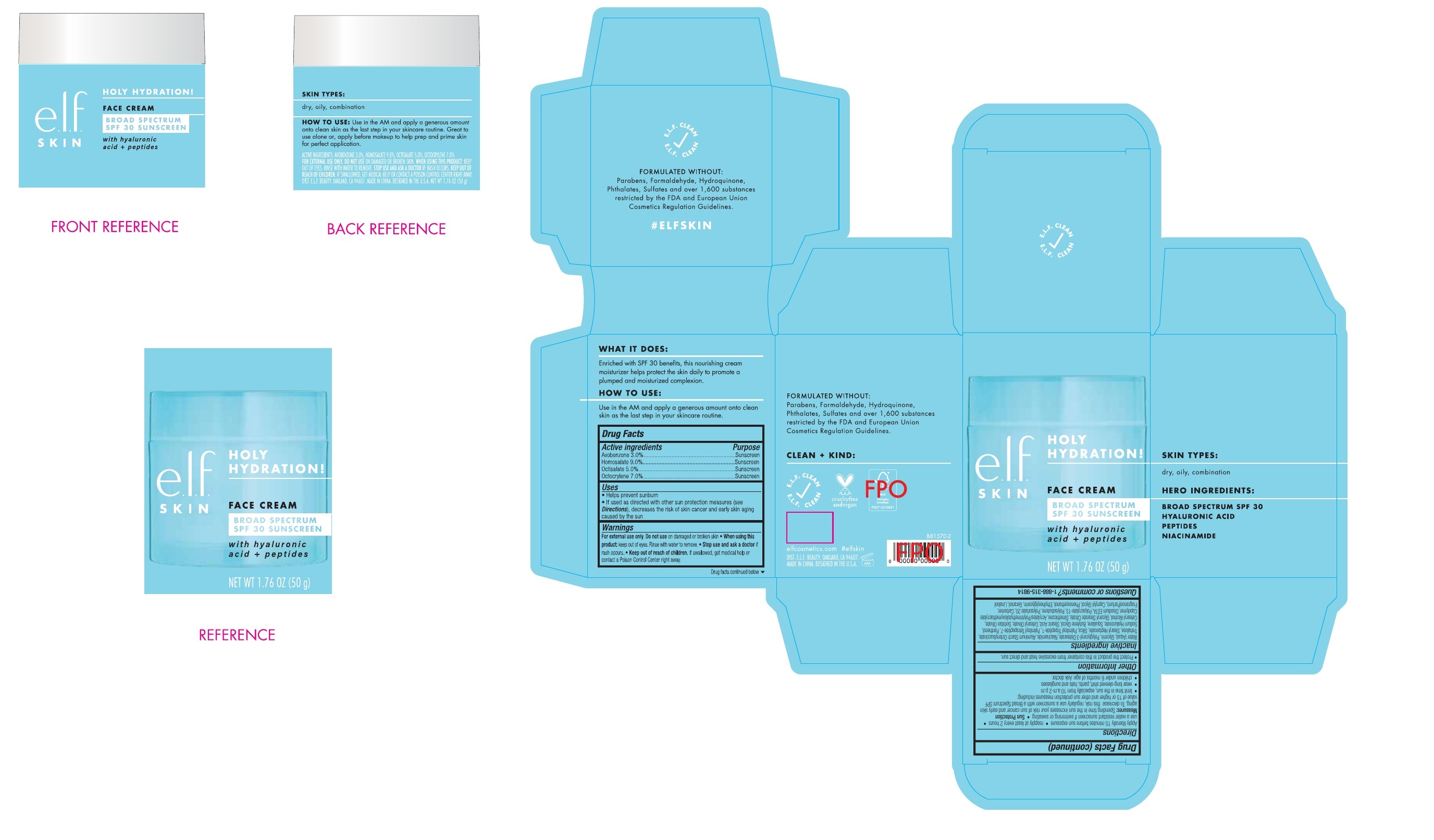 DRUG LABEL: e.l.f. Holy Hydration Face Cream SPF 30 Sunscreen
NDC: 76354-441 | Form: CREAM
Manufacturer: e.l.f. Cosmetics, Inc
Category: otc | Type: HUMAN OTC DRUG LABEL
Date: 20241106

ACTIVE INGREDIENTS: AVOBENZONE 30 mg/1 g; HOMOSALATE 90 mg/1 g; OCTISALATE 50 mg/1 g; OCTOCRYLENE 70 mg/1 g
INACTIVE INGREDIENTS: WATER; GLYCERIN; POLYGLYCERYL-3 DISTEARATE; NIACINAMIDE; ALUMINUM STARCH OCTENYLSUCCINATE; TREHALOSE; STEARYL HEPTANOATE; SILICON DIOXIDE; PALMITOYL TRIPEPTIDE-1; PALMITOYL TETRAPEPTIDE-7; PANTHENOL; HYALURONATE SODIUM; SQUALANE; BUTYLENE GLYCOL; STEARIC ACID; CETEARYL OLIVATE; SORBITAN OLIVATE; CETOSTEARYL ALCOHOL; GLYCERYL STEARATE CITRATE; DIMETHICONE; EDETATE DISODIUM ANHYDROUS; POLYSORBATE 20; CARBOMER HOMOPOLYMER, UNSPECIFIED TYPE; CAPRYLYL GLYCOL; PHENOXYETHANOL; ETHYLHEXYLGLYCERIN; GERANIOL; LINALOOL, (+/-)-

e.l.f. Holy Hydration Face Cream SPF 30 Sunscreen

Active ingredients

Avobenzone 3.0%

Homosalate 9.0%

Octisalate 9.0%

Octocrylene 7.0%

Purpose

Sunscreen

Uses

Helps prevent sunburn

If used as directed with other sun protection measures (see), decreases the risk of skin cancer and early skin aging caused by the sun Directions

Warnings

For external use only

Do not use

on damaged or broken skin

When using this product

keep out of eyes. Rinse with water to remove.

Stop use and ask a doctor

if rash occurs

Keep out of reach of children.

If swallowed, get medical help or contact a Poison Control Center right away.

Directions

- Apply liberally 15 minutes before sun exposure
- reapply at least every 2 hours
- use a water resistant sunscreen if swimming or sweating
- Spending time in the sun increases your risk of sun cancer and early skin aging. To decrease this risk, regularly use a sunscreen with a Broad Spectrum SPF value of 15 or higher and other sun protection measures including: Sun Protection Measures:
- limit time in the sun, especially from 10 a.m.-2 p.m.
- wear long-sleeved shirt, pants, hats and sunglasses
- children under 6 months of age: Ask doctor.

Other Information

- Protect the product in this container from excessive heat and direct sun.

Inactive ingredients

Water (Aqua), Glycerin, Polyglyceryl-3 Distearate, Niacinamide, Aluminum Starch Octenylsuccinate, Trehalose, Stearyl Heptanoate, Silica, Palmitoyl Tripeptide-1, Palmitoyl Tetrapeptide-7, Panthenol, Sodium Hyaluronate, Squalane, Butylene Glycol, Stearic Acid, Cetearyl Olivate, Sorbitan Olivate, Cetearyl Alcohol, Glyceryl Stearate Citrate, Dimethicone, Acrylates/Polytrimethylsiloxymethacrylate Copolymer, Disodium EDTA, Polyacrylate-13, Polyisobutene, Polysorbate 20, Carbomer, Fragrance(Parfum), Caprylyl Glycol, Phenoxyethanol, Ethylhexylglycerin, Geraniol, Linalool

Questions or comments?

1-888-315-9814